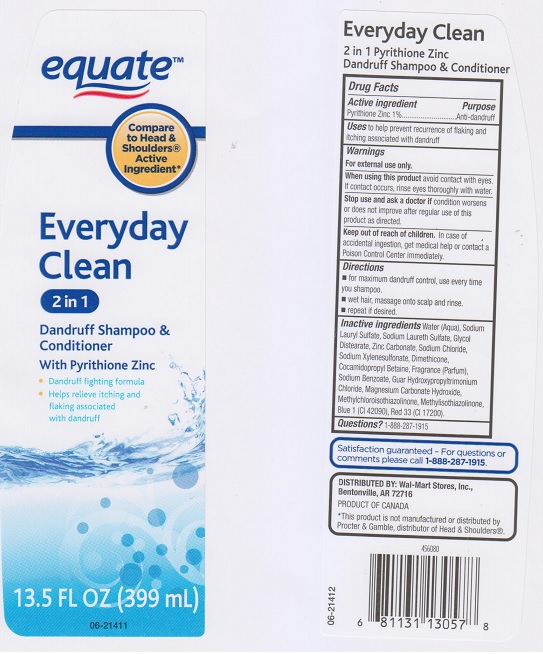 DRUG LABEL: EQUATE EVERYDAY CLEAN 2IN1 DANDRUFF
NDC: 49035-424 | Form: SHAMPOO
Manufacturer: WAL-MART STORES INC
Category: otc | Type: HUMAN OTC DRUG LABEL
Date: 20160711

ACTIVE INGREDIENTS: PYRITHIONE ZINC 10 mg/1 mL
INACTIVE INGREDIENTS: WATER; SODIUM LAURYL SULFATE; SODIUM LAURETH-3 SULFATE; GLYCOL DISTEARATE; ZINC CARBONATE; SODIUM CHLORIDE; SODIUM XYLENESULFONATE; DIMETHICONE; COCAMIDOPROPYL BETAINE; SODIUM BENZOATE; GUAR HYDROXYPROPYLTRIMONIUM CHLORIDE (1.7 SUBSTITUENTS PER SACCHARIDE); MAGNESIUM CARBONATE HYDROXIDE; METHYLCHLOROISOTHIAZOLINONE; METHYLISOTHIAZOLINONE; FD&C BLUE NO. 1; D&C RED NO. 33

DRUG FACTS

Active ingredient

Pyrithione Zinc 1%

Purpose

Anti-dandruff

Uses

to help prevent recurrence of flaking and itching associated with dandruff.

Warnings

For external use only.

When using this product

avoid contact with eyes. If contact occurs, rinse eyes thoroughly with water.

Stop use and ask a doctor if

condition worsens or does not improve after regular use of this product as directed.

Keep out of reach of children.

In case of accidental ingestion, get medical help or contact a Poison Control Center immediately.

Directions

- for maximum dandruff control use every time you shampoo.
- wet hair, massage onto scap and rinse.
- repeat if desired.

Inactive ingredients

Water (Aqua), Sodium Lauryl Sulfate, Sodium Laureth Sulfate, Glycol Distearate, Zinc Carbonate, Sodium Chloride, Sodium Xylenesulfonate, Dimethicone, Cocamidopropyl Betaine, Fragrance (Parfum), Sodium Benzoate, Guar Hydropropyltrimonium Chloride, Magnesium Carbonate Hydroxide , Methylchloroisothiazolinone, Methylisothiazolinone, Blue 1 (CI 42090), Red 33 (CI 17200).

Questions?

1-888-287-1915